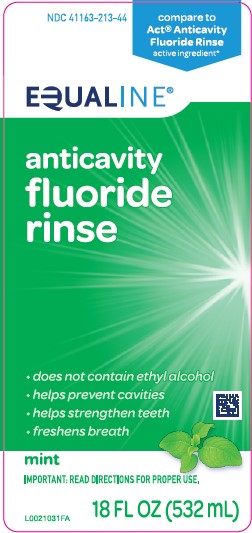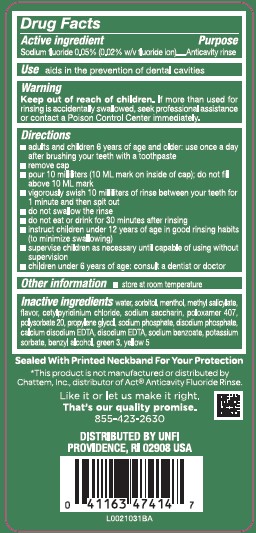 DRUG LABEL: Anticavity Fluoride Rinse
NDC: 41163-213 | Form: MOUTHWASH
Manufacturer: United Natural Foods, Inc. dba UNFI
Category: otc | Type: HUMAN OTC DRUG LABEL
Date: 20260216

ACTIVE INGREDIENTS: SODIUM FLUORIDE 0.2 mg/1 mL
INACTIVE INGREDIENTS: WATER; SORBITOL; MENTHOL; METHYL SALICYLATE; CETYLPYRIDINIUM CHLORIDE; SACCHARIN SODIUM; POLOXAMER 407; POLYSORBATE 20; PROPYLENE GLYCOL; SODIUM PHOSPHATE; SODIUM PHOSPHATE, DIBASIC, ANHYDROUS; EDETATE CALCIUM DISODIUM ANHYDROUS; EDETATE DISODIUM ANHYDROUS; SODIUM BENZOATE; POTASSIUM SORBATE; BENZYL ALCOHOL; FD&C GREEN NO. 3; FD&C YELLOW NO. 5

Equaline 213.001/213AE rev 2
Anticavity Fluoride Rinse, Mint

Active ingredient

Sodium fluoride 0.05% (0.02% w/v fluoride ion)

Purpose

Anticavity rinse

Use

aids in the prevention of dental cavities

Warning

for this product

Keep out of reach of children.

If more than used for rinsing is accidentally swallowed, seek professional assistance or contact a Poison Control Center immediately.

Directions

- adults and children 6 years of age and older: use once a day after brushing your teeth with a toothpaste
- remove cap
- pour 10 milliliters (10 ML mark on inside of cap); do not fill above 10 ML mark
- vigorously swish 10 milliliters of rinse between your teeth for 1 minute and then spit out
- do not swallow the rinse
- do not eat or drink for 30 minutes after rinsing
- instruct children under 12 years of age in good rinsing habits (to minimize swallowing)
- supervise children as necessary until capable of using without supervision
- children under 6 years of age: consult a dentist or doctor

Other information

- store at room temperature

Inactve ingredients

water, sorbitol, menthol, methyl salicylate, flavor, cetylpyridinium chloride, sodium saccharin, poloxamer 407, polysorbate 20, propylene glycol, sodium phosphate, disodium phosphate, calcium disodium EDTA, disodium EDTA, sodium benzoate, potassium sorbate, benzyl alcohol, green 3, yellow 5

ADVERSE REACTION

Sealed with printed neckband for your protection

*This product is not manufactured or distributed by Chattem, Inc., distributor of Act®Anticavity Fluoride Rinse.

Like it or let us make it right.

That's our quality promise.

855-423-2630

DISTRIBUTED BY UNFI

PROVIDENCE, RI 02908 USA

Principal Panel Display

NDC 41163-213-44

comapre to Act®Anticavity Fluoride Rinse active ingredient*

EQUALINE®

anticavity

fluoride

rinse

- does not contain ethyl alcohol
- helps prevent cavities
- helps strengthen teeth
- freshens breath

mint

INPORTANT: READ DIRECTIONS FOR PROPER USE.

18 FL OZ (532 mL)